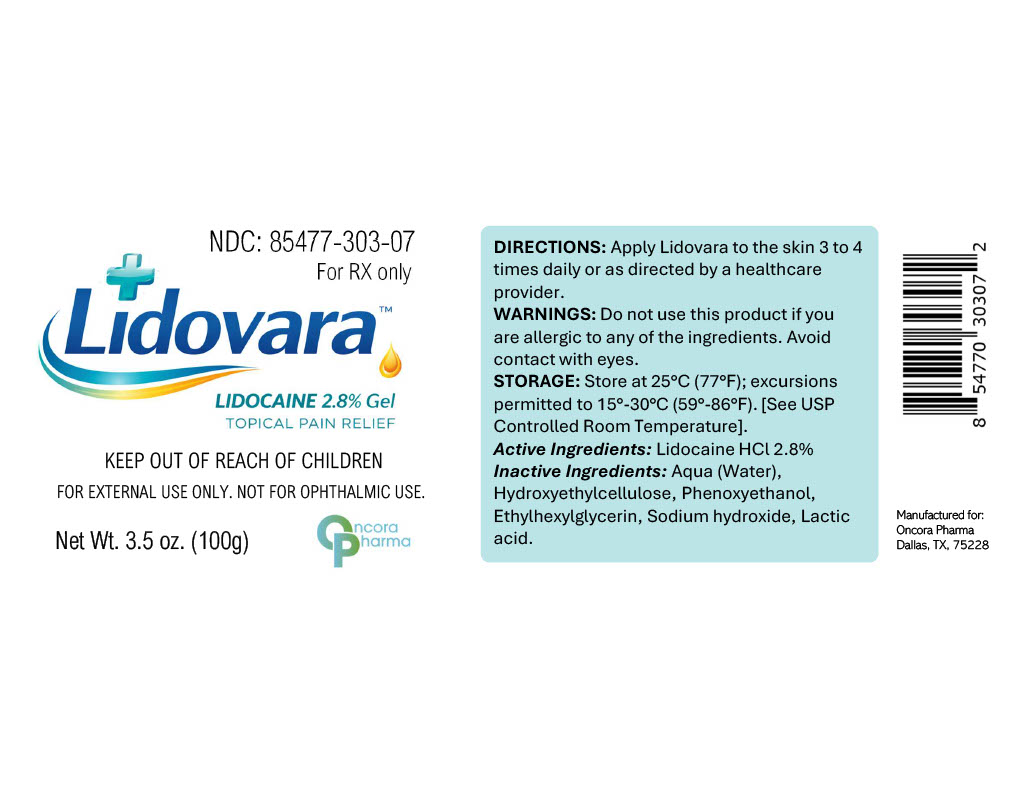 DRUG LABEL: Lidovara
NDC: 85477-303 | Form: GEL
Manufacturer: Oncora Pharma, LLC
Category: prescription | Type: HUMAN PRESCRIPTION DRUG LABEL
Date: 20260227

ACTIVE INGREDIENTS: LIDOCAINE 28 mg/1 g
INACTIVE INGREDIENTS: WATER; HYDROXYETHYLCELLULOSE; PHENOXYETHANOL; ETHYLHEXYLGLYCERIN; SODIUM HYDROXIDE; LACTIC ACID

Lidovara™ 2.8% Gel

DESCRIPTION

Lidovara™ is a topical gel containing Lidocaine Hydrochloride 28 mg/g (2.8%).

INDICATIONS AND USAGE

Lidovara™ is indicated for topical analgesia as directed by a healthcare provider.

CONTRAINDICATIONS

Lidovara™ is contraindicated in patients with known hypersensitivity to lidocaine or any component of the formulation.

WARNINGS

For external use only. Not for ophthalmic use.
Avoid contact with eyes.
Excessive application may result in increased systemic absorption.
Keep out of reach of children.

OVERDOSAGE

Excessive topical application may result in increased systemic absorption of lidocaine. In the event of overdose, discontinue use and seek medical attention.

DOSAGE AND ADMINISTRATION

For topical use only.
Apply to the affected area 3 to 4 times daily or as directed by a healthcare provider.

HOW SUPPLIED

Lidovara™ (Lidocaine Hydrochloride 28 mg/g) is supplied as a clear topical gel in a 3.5 oz (100 g) tube.
NDC 85477-303-07

PRINCIPAL DISPLAY PANEL

pdp